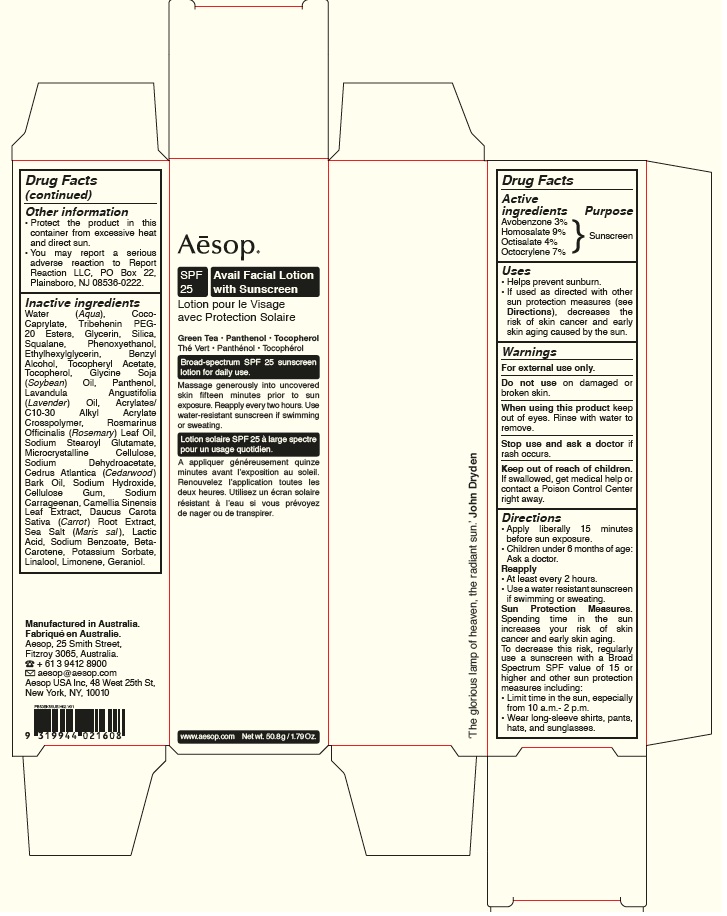 DRUG LABEL: Avail Facial Sunscreen SPF 25
NDC: 76293-055 | Form: LOTION
Manufacturer: Emeis Cosmetics Pty Ltd
Category: otc | Type: HUMAN OTC DRUG LABEL
Date: 20251217

ACTIVE INGREDIENTS: HOMOSALATE 90 mg/1 g; OCTISALATE 40 mg/1 g; AVOBENZONE 30 mg/1 g; OCTOCRYLENE 70 mg/1 g
INACTIVE INGREDIENTS: LACTIC ACID, L-; SEA SALT; POTASSIUM SORBATE; TRIBEHENIN PEG-20 ESTERS; GLYCERIN; SILICON DIOXIDE; SQUALANE; SODIUM HYDROXIDE; SOYBEAN OIL; CARBOMER COPOLYMER TYPE A; CEDRUS ATLANTICA BARK OIL; .ALPHA.-TOCOPHEROL ACETATE, D-; SODIUM BENZOATE; .BETA.-CAROTENE; GERANIOL; ETHYLHEXYLGLYCERIN; BENZYL ALCOHOL; SODIUM DEHYDROACETATE; CARROT; LIMONENE, (+/-)-; SODIUM STEAROYL GLUTAMATE; COCO-CAPRYLATE; PHENOXYETHANOL; MICROCRYSTALLINE CELLULOSE; CARBOXYMETHYLCELLULOSE SODIUM; CARRAGEENAN; LAVENDER OIL; WATER; TOCOPHEROL; PANTHENOL; ROSEMARY OIL; GREEN TEA LEAF; LINALOOL, (+/-)-

Avail Facial Sunscreen SPF 25

Active ingredients

Avobenzone 3%

Homosalate 9%

Octisalate 4%

Octocrylene 7%

Purpose

Sunscreen

Uses

- Helps prevent sunburn
- if used as directed with other sun protection measures (see Directions), decreases the risk of skin cancer and early skin aging caused by the sun.

Warnings

For external use only.

Do not use

on damaged or broken skin.

When using this product

keep out of eyes. Rinse with water to remove.

Stop use and ask a doctor

if rash occurs.

Keep out of reach of children.

If swallowed, get medical help or contact a Poison Control Center right away.

Directions

- Apply liberally 15 minutes before sun exposure.
- Children under 6 months: Ask a doctor.

Reapply

- At least every 2 hours.
- Use a water resistant sunscreen if swimming or sweating.

Sun Protection Measures. Spending time in the sun increases your risk of skin cancer and early skin aging. To decrease this risk, regularly use a sunscreen with a Broad Spectrum SPF value of 15 or higher and other sun protection measures including:

- Limit time in the sun, especially from 10 a.m.- 2 p.m.
- Wear long-sleeve shirts, pants, hats and sunglasses.

Other information

- Protect the product in this container from excessive heat and direct sun.
- You may report a serious adverse reaction to Report Reaction, LLC, P.O. Box 22, Plainsboro, NJ 08536-0222.

Inactive ingredients

Water (Aqua), Coco-Caprylate, Tribehenin PEG-20 Esters, Glycerin, Silica, Squalane, Phenoxyethanol, Ethylhexylglycerin, Benzyl Alcohol, Tocopheryl Acetate, Tocopherol, Glycine Soja (Soybean) Oil, Panthenol, Lavandula Angustifolia (Lavender) Oil, Acrylates/C10-30 Alkyl Acrylate Crosspolymer, Rosmarinus Officinalis (Rosemary) Leaf Oil, Sodium Stearoyl Glutamate, Microcrystalline Cellulose, Sodium Dehydroacetate, Cedrus Atlantica (Cedarwood) Bark Oil, Sodium Hydroxide, Cellulose Gum, Sodium Carrageenan, Camellia Sinensis Leaf Extract, Daucus Carota Sativa (Carrot) Root Extract, Sea Salt (Maris sal), Lactic Acid, Sodium Benzoate, Beta-Carotene, Potassium Sorbate, Linalool, Limonene, Geraniol.

Company information

Aesop, 25 Smith Street, Fitzroy 3065, Australia.

+61 3 9412 8900

aesop@aesop.com

Aesop USA Inc, 48 West 25th St, New York, NY, 10010

Product Packaging - 50.8g

Aēsop

Avail Facial Lotion with Sunscreen SPF 25

Green Tea · Panthenol · Tocopherol

Broad-spectrum SPF 25 sunscreen lotion for daily use.

Massage generously into uncovered skin fifteen minutes prior to sun exposure. Reapply every two hours. Use water-resistant sunscreen if swimming or sweating.

www.aesop.com

Net wt. 50.8g/1.79Oz.